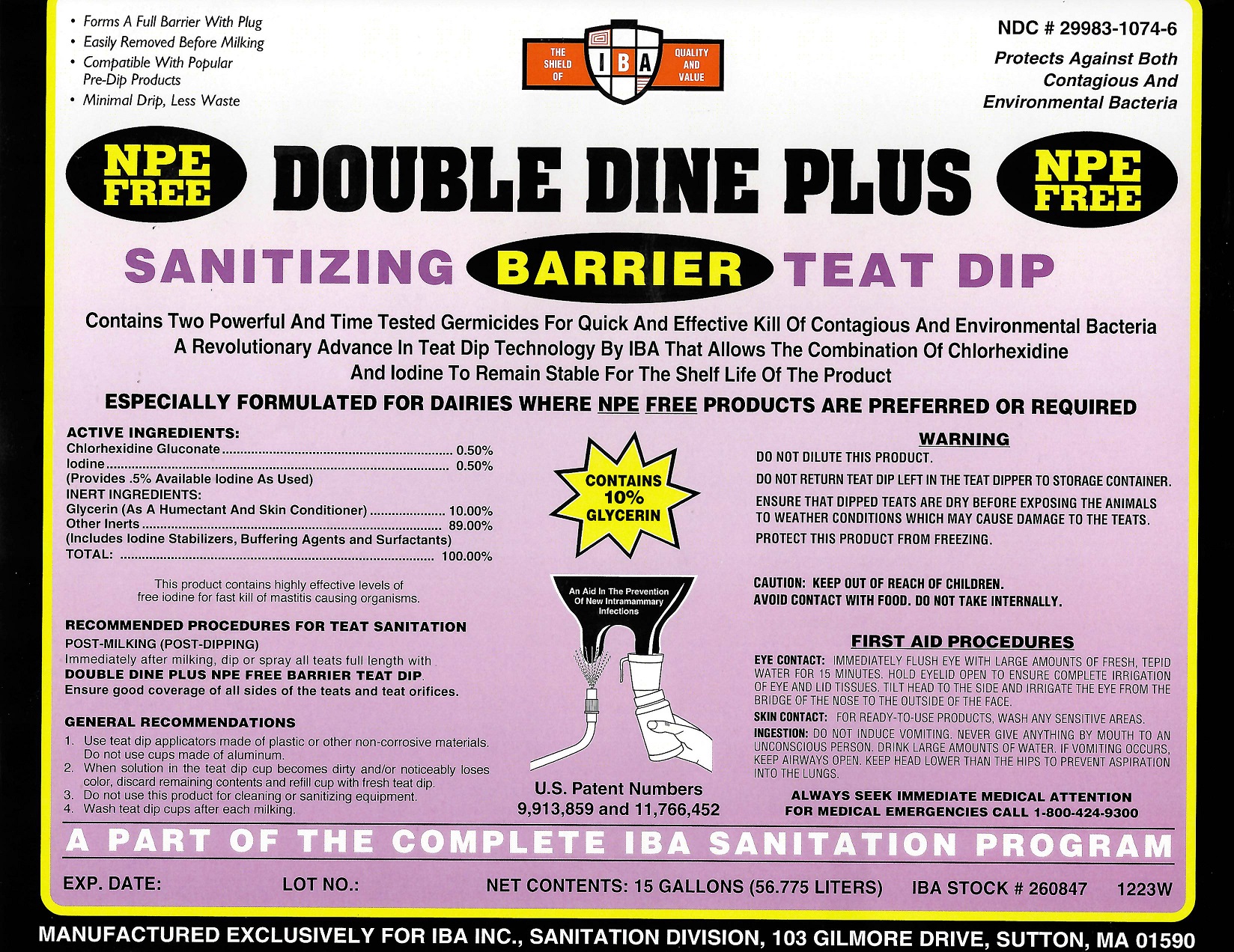 DRUG LABEL: Double Dine Plus Barrier NPE Free
NDC: 29983-1074 | Form: LIQUID
Manufacturer: IBA
Category: animal | Type: OTC ANIMAL DRUG LABEL
Date: 20251126

ACTIVE INGREDIENTS: IODINE 0.5 kg/100 kg; CHLORHEXIDINE GLUCONATE 0.5 kg/100 kg

Double Dine Plus Barrier NPE Free

ACTIVE INGREDIENTS

ACTIVE INGREDIENT:

CHLORHEXIDINE GLUCONATE......................................................0.50%
IODINE.....................................................................................0.50%
(PROVIDES A Full .5% AVAILABLE IODINE AS USED)

INERT INGREDIENTS

GLYCERIN(AS A HUMECTANT AND SKIN CONDITIONER)...............10.00%
OTHER INERTS.........................................................................89.00%
(INCLUDES IODINE STABILIZERS, BUFFERING AGENTS AND SURFACTANTS)
TOTAL:.....................................................................................100.00%

THIS PRODUCT CONTAINS HIGHLY EFFECTIVE LEVELS OF
FREE IODINE FOR FAST KILL OF MASTITIS CAUSING ORGANISMS.

INDICATIONS AND USAGE

GENERAL RECOMMENDATIONS
1. Use teat dip applicators made of plastic or other non-corrosive materials. Do not use cups made of aluminum.
2. When solution in the teat dip cup becomes dirty and/or noticeably loses color, discard remaining contents and refill cup with fresh teat dip.
3. Do not use this product for cleaning or sanitizing equipment
4. Wash Teat Dip cups after each milking.
RECOMMENDED PROCEDURES FOR TEAT SANITATION
POST-MILKING (POST-DIPPING)
Immediately after milking, dip or spray all teats full length with DOUBLE DINE NPE FREE BARRIER TEAT DIP. Ensure good coverage of all sides of the teats and teat orifices.

WARNINGS

DO NOT DILUTE THIS PRODUCT.

DO NOT RETURN TEAT DIP LEFT IN THE TEAT DIPPER TO STORAGE CONTAINER.

ENSURE THAT DIPPED TEATS ARE DRY BEFORE EXPOSING THE ANIMALS TO WEATHER CONDITIONS WHICH MAY CAUSE DAMAGE TO THE TEATS.
PROTECT THIS PRODUCT FROM FREEZING.

CAUTION: KEEP OUT OF REACH OF CHILDREN.
AVOID CONTACT WITH FOOD. DO NOT TAKE INTERNALLY.

FIRST AID PROCEDURES

EYE CONTACT: IMMEDIATELY FLUSH EYE WITH LARGE AMOUNTS OF FRESH, TEPID WATER FOR 15 MINUTES. HOLD EYELID OPEN TO ENSURE COMPLETE IRRIGATION OF EYE AND LID TISSUES. TILT HEAD TO THE SIDE AND IRRIGATE THE EYE FROM THE BRIDGE OF THE NOSE TO THE OUTSIDE OF THE FACE.
SKIN CONTACT: FOR READY TO USE PRODUCTS, WASH ANY SENSITIVE AREAS.
INGESTION:DO NOT INDUCE VOMITING. NEVER GIVE ANYTHING BY MOUTH TO AN UNCONSCIOUS PERSON. DRINK LARGE AMOUNTS OF WATER. IF VOMITING OCCURS KEEP AIRWAYS OPEN. KEEP HEAD LOWER THAN THE HIPS TO PREVENT ASPIRATION INTO THE LUNGS.

ALWAYS SEEK IMMEDIATE MEDICAL ATTENTION
FOR MEDICAL EMERGENCIES CALL 1-800-424-9300

FIRST AID PROCEDURES

EYE CONTACT: IMMEDIATELY FLUSH EYE WITH LARGE AMOUNTS OF FRESH, TEPID WATER FOR 15 MINUTES. HOLD EYELID OPEN TO ENSURE COMPLETE IRRIGATION OF EYE AND LID TISSUES. TILT HEAD TO THE SIDE AND IRRIGATE THE EYE FROM THE BRIDGE OF THE NOSE TO THE OUTSIDE OF THE FACE.
SKIN CONTACT: FOR READY TO USE PRODUCTS, WASH ANY SENSITIVE AREAS.
INGESTION:DO NOT INDUCE VOMITING. NEVER GIVE ANYTHING BY MOUTH TO AN UNCONSCIOUS PERSON. DRINK LARGE AMOUNTS OF WATER. IF VOMITING OCCURS KEEP AIRWAYS OPEN. KEEP HEAD LOWER THAN THE HIPS TO PREVENT ASPIRATION INTO THE LUNGS.

ALWAYS SEEK IMMEDIATE MEDICAL ATTENTION
FOR MEDICAL EMERGENCIES CALL 1-800-424-9300